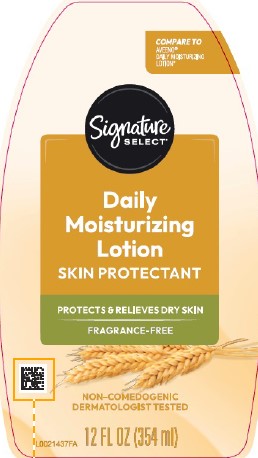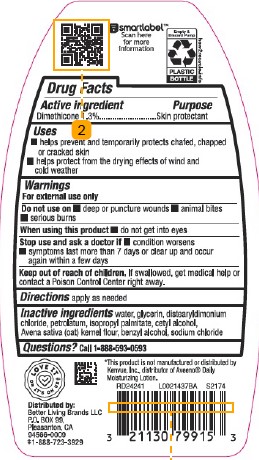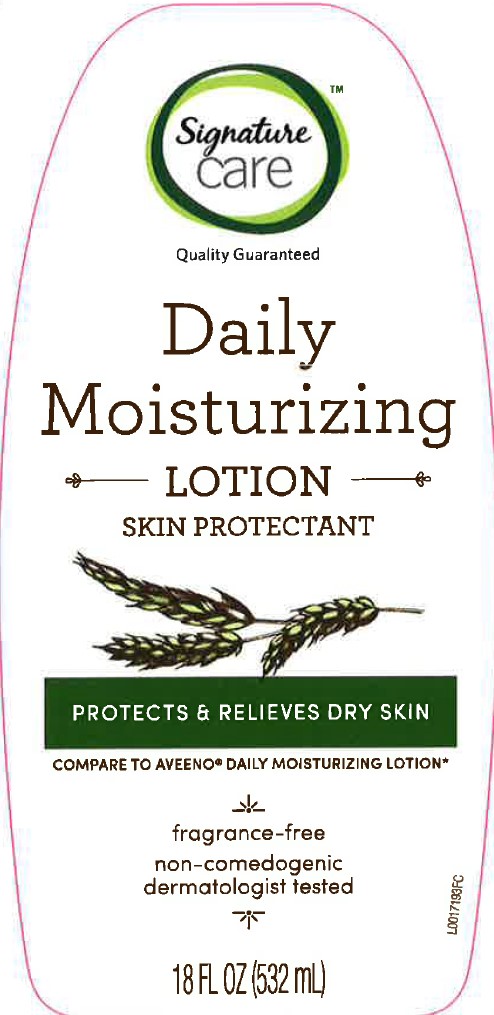 DRUG LABEL: Oatmeal
NDC: 21130-898 | Form: LOTION
Manufacturer: Better Living Brands, LLC
Category: otc | Type: HUMAN OTC DRUG LABEL
Date: 20260223

ACTIVE INGREDIENTS: DIMETHICONE 13 mg/1 mL
INACTIVE INGREDIENTS: WATER; GLYCERIN; DISTEARYLDIMONIUM CHLORIDE; PETROLATUM; ISOPROPYL PALMITATE; CETYL ALCOHOL; OATMEAL; BENZYL ALCOHOL; SODIUM CHLORIDE

Signature Care_Signature Select 619.003/619AC rev 2
Daily Moisturizing Lotion

smartlabel ™

Scan her for more information

Empty & Discard Pump

PLASTIC BOTTLE

how2recycle.info

active ingredient

Dimethicone 1.3%

Purpose

skin protectant

Uses

- helps prevent and temporarily protects chafed, chapped or cracked skin
- helps protect from the drying effects of wind and cold weather

Warnings

For external use only

Do not use on

- deep puncture wounds
- animal bites
- serious burns

When using this product

- do not get into eyes

Stop use and ask a doctor if

- condition worsens
- symptoms last more than 7 days or clear up and occur again within a few days

Keep out of reach of children.

If swallowed, get medical help or contact a Poison Control Center right away.

Directions

apply as needed

Inactive ingredients

water, glycerin, distearyldimonium chloride, petrolatum, isopropyl palmitate, cetyl alcohol, Avena sativa (oat) kernel flour, benzyl alcohol, sodium chloride

Questions?

Call 1-888-593-0593

adverse reaction

*This product is not manufactured or distributed by Kenvue, Inc., distributor of Aveeno®Active Daily Moisturizing Lotion.

LOVE IT OR IT'S ON US ‡

DISTRIBUTED BY BETTER LIVING BRANDS LLC

P.O. BOX 99

PLEASANTON, CA

94566-0009

1-888-723-3929

principal display panel

Signature

CARE

Quality Guaranteed

Daily

Moisturizing

LOTION

SKIN PROTECTANT

PROTECTS & RELIEVES DRY SKIN

COMPARE TO AVEENO DAILY MOISTURIZING LOTION

fragrance-free

non-comedogenic

dermatologist tested

18 FL OZ (532 mL)

principal display panel

COMPARE TO AVEENO®DAILY MOISTURIZING LOTION*

Signature Select®

Daily Moisturizing Lotion

SKIN PROTECTANT

PROTECTS & RELIEVES DRY SKIN

FRAGRANCE-FREE

NON-COMEDOGENIC

DERMATOLOGIST TESTED

12 FL OZ (354 ml)